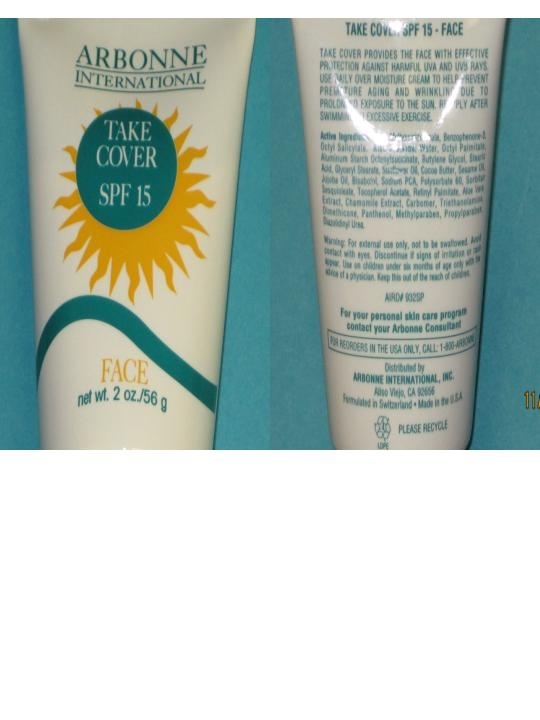 DRUG LABEL: MOISTURIZING SUNSCREEN SPF15
NDC: 59663-001 | Form: LOTION
Manufacturer: Shine & Pretty (USA), Corp.
Category: otc | Type: HUMAN OTC DRUG LABEL
Date: 20110602

ACTIVE INGREDIENTS: OXYBENZONE 1 mL/100 mL; OCTINOXATE 1 mL/200 mL
INACTIVE INGREDIENTS: SORBITAN SESQUIOLEATE; POLYSORBATE 60; CARBOMER 934; VITAMIN E ACETATE; STEARIC ACID; PROPYLENE GLYCOL; VITAMIN A PALMITATE; PROPYLPARABEN; TROLAMINE; GLYCERYL MONOSTEARATE; ALOE VERA LEAF; WATER; DIAZOLIDINYL UREA; ETHYLHEXYL PALMITATE; ALUMINUM STARCH OCTENYLSUCCINATE; METHYLPARABEN; CHAMAEMELUM NOBILE FLOWER

PURPOSE

For Sun protection: Apply on surfaces of skin, on face, arm and hand. SPF-15 provides the face and body skin with effective protection against harmful UVA and UVB rays. Use daily over moisture cream to help prevent premature aging and wrinkling due to prolonged exposure to the sun, reapply after swimming or excessive exercise.

INDICATIONS AND USAGE

Smear Lightly.

WARNINGS

Warning: For external use only, not to be swallowed. Avoid contact with eye. Discontinue if signs of irritation or rash appear.

DOSAGE AND ADMINISTRATION

To Apply lightly.

INACTIVE INGREDIENT

Inactive Ingredients: SORBITAN SESQUIOLEATE, POLYSORBATE 60, CARBOMER 934, VITAMIN E ACETATE, STEARIC ACID, PROPYLENE GLYCOL, VITAMIN A PALMITATE, PROPYLPARABEN, Water.

KEEP OUT OF REACH OF CHILDREN

Keep Out of the reach of children. Use on children under six months of age only with the advice of a physician.

ACTIVE INGREDIENT

OXYBENZONE and OCTINOXATE.

PACKAGE LABEL

MM1